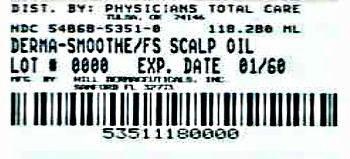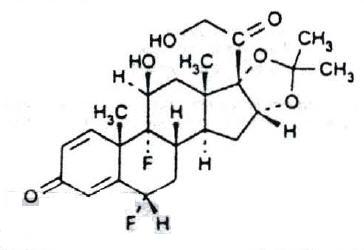 DRUG LABEL: Derma-Smoothe/FS
NDC: 54868-5351 | Form: OIL
Manufacturer: Physicians Total Care, Inc.
Category: prescription | Type: HUMAN PRESCRIPTION DRUG LABEL
Date: 20120601

ACTIVE INGREDIENTS: fluocinolone acetonide 0.11 mg/1 mL
INACTIVE INGREDIENTS: peanut oil; light mineral oil; isopropyl myristate; isopropyl alcohol; OLETH-2

Derma-Smoothe/FS® fluocinolone acetonide Topical Oil, 0.01%
(Scalp Oil)

For Topical Use Only-
Not for Oral, Ophthalmic, or Intravaginal Use

DESCRIPTION

Derma-Smoothe/FSTopical® Oil contains fluocinolone acetonide {(6α, 11β, 16α)-6,9-difluoro-11,21-dihydroxy-16,17[(1-methylethylidene)bis(oxy)]-pregna-1,4-diene-3,20-dione, cyclic 16,17 acetal with acetone}, a synthetic corticosteroid for topical dermatologic use. This formulation is also marketed as Derma-Smoothe/FS® 0.01% fluocinolone acetonide for use as body oil for atopic dermatitis in adults and for moderate to severe atopic dermatitis in pediatric patients 2 years and older, and as fluocinolone acetonide oil, 0.01% for chronic eczematous external otitis. Chemically, fluocinolone acetonide is C24H30F2O6. It has the following structural formula:

Fluocinolone acetonide in Derma-Smoothe/FS® has a molecular weight of 452.50. It is a white crystalline powder that is odorless, stable in light, and melts at 270°C with decomposition; soluble in alcohol, acetone and methanol; slightly soluble in chloroform; insoluble in water.

Each gram of Derma-Smoothe/FS® contains approximately 0.11 mg of fluocinolone acetonide in a blend of oils, which contains isopropyl alcohol, isopropyl myristate, light mineral oil, oleth-2, refined peanut oil NF and fragrances .

Each packaged product contains 2 shower caps. The shower cap is made of low density polyethylene material with rubber elastic.

CLINICAL PHARMACOLOGY

Like other topical corticosteroids, fluocinolone acetonide has anti-inflammatory, antipruritic, and vasoconstrictive properties. The mechanism of the anti-inflammatory activity of the topical steroids, in general, is unclear. However, corticosteroids are thought to act by the induction of phospholipase A2 inhibitory proteins, collectively called lipocortins. It is postulated that these proteins control the biosynthesis of potent mediators of inflammation such as prostaglandins and leukotrienes by inhibiting the release of their common precursor arachidonic acid. Arachidonic acid is released from membrane phospholipids by phospholipase A2.

Pharmacokinetics

The extent of percutaneous absorption of topical corticosteroids is determined by many factors including the vehicle and the integrity of the epidermal barrier. Occlusion of topical corticosteroids can enhance penetration. Topical corticosteroids can be absorbed from normal intact skin. Also, inflammation and/or other disease processes in the skin can increase percutaneous absorption.

Derma-Smoothe/FS® is in the low to medium range of potency as compared with other topical corticosteroids.

CLINICAL STUDIES

In a vehicle-controlled study for the treatment of psoriasis of the scalp in adults, after 21 days of treatment, 60% of patients on active treatment and 21% of patients on the drug vehicle had excellent to cleared clinical response.

Open-label safety studies on 33 children (20 subjects ages 2 to 6 years, 13 subjects ages 7 to 12 years) with moderate to severe stable atopic dermatitis, and baseline body surface area involvement greater than 75% in 18 patients, and 50% to 75% in 15 patients, were treated with Derma-Smoothe/FS® twice daily for 4 weeks. Morning pre-stimulation cortisol level and post-Cortrosyn stimulation cortisol level were obtained in each subject at the beginning of the trial and at the end of 4 weeks of treatment. At the end of treatment, 4 out of 18 subjects aged 2 to 5 years showed low pre-stimulation cortisol levels (3.2 to 6.6 ug/dL; normal: cortisol > 7 ug/dL) but all had normal responses to 0.25 mg of Cortrosyn stimulation (cortisol > 18 ug/dL).

A clinical study was conducted to assess the safety of Derma-Smoothe/FS®, which contains refined peanut oil, on subjects with known peanut allergies. The study enrolled 13 patients with atopic dermatitis, 6 to 17 years of age. Of the 13 patients, 9 were Radioallergosorbent Test (RAST) positive to peanuts and 4 had no peanut sensitivity (controls). The study evaluated the responses to both prick test and patch test utilizing refined peanut oil NF, Derma-Smoothe/FS® and histamine/saline controls, on the 13 individuals. These subjects were also treated with Derma-Smoothe/FS® twice daily for 7 days. Prick test and patch test results for all 13 patients were negative to Derma-Smoothe/FS® and the refined peanut oil. One of the 9 peanut-sensitive patients experienced an exacerbation of atopic dermatitis after 5 days of Derma-Smoothe/FS® use. Importantly, the bulk peanut oil NF, used in Derma-Smoothe/FS® is heated at 475° F for at least 15 minutes, which should provide for adequate decomposition of allergenic proteins.

INDICATION AND USAGE

Derma-Smoothe/FS® is a low to medium potency corticosteroid indicated:

In adult patients for the treatment of psoriasis of the scalp (Scalp Oil).

CONTRAINDICATIONS

Derma-Smoothe/FS® is contraindicated in those patients with a history of hypersensitivity to any of the components of the preparation.

This product contains refined peanut oil NF (see PRECAUTIONS section).

PRECAUTIONS

General

Systemic absorption of topical corticosteroids can produce reversible hypothalamic-pituitary-adrenal (HPA) axis suppression with the potential for glucocorticosteroid insufficiency after withdrawal of treatment. Manifestations of Cushing's syndrome, hyperglycemia, and glucosuria can also be produced in some patients by systemic absorption of topical corticosteroids while on treatment.

Patients applying a topical steroid to a large surface area or to areas under occlusion should be evaluated periodically for evidence of HPA axis suppression. This may be done by using the ACTH stimulation, A.M. plasma cortisol, and urinary free cortisol tests.

If HPA axis suppression is noted, an attempt should be made to withdraw the drug, to reduce the frequency of application, or to substitute a less potent corticosteroid. Infrequently, signs and symptoms of glucocorticoid insufficiency may occur requiring supplemental systemic corticosteroids. For information on systemic supplementation, see prescribing information for those products.

Children may be more susceptible to systemic toxicity from equivalent doses due to their larger skin surface to body mass ratios. (See PRECAUTIONS-Pediatric use)

Allergic contact dermatitis to any component of topical corticosteroids is usually diagnosed by a failure to heal rather than noting a clinical exacerbation, which may occur with most topical products not containing corticosteroids. Such an observation should be corroborated with appropriate diagnostic testing. One peanut sensitive child experienced a flare of his atopic dermatitis after 5 days of twice daily treatment with Derma-Smoothe/FS® (see CLINICAL STUDIES section).

If wheal and flare type reactions (which may be limited to pruritus) or other manifestations of hypersensitivity develop, Derma-Smoothe/FS® should be discontinued immediately and appropriate therapy instituted.

If concomitant skin infections are present or develop, an appropriate antifungal or antibacterial agent should be used. If a favorable response does not occur promptly, use of Derma-Smoothe/ FS® should be discontinued until the infection has been adequately controlled.

Derma-Smoothe/FS® is formulated with 48% refined peanut oil NF. Peanut oil used in this product is routinely tested for peanut proteins through amino acid analysis; the quantity of amino acids is below 0.5 parts per million (ppm). Physicians should use caution in prescribing Derma-Smoothe/FS® for peanut sensitive individuals.

Information for Patients

Patients using topical corticosteroids should receive the following information and instructions:

1. This medication is to be used as directed by the physician. It is for external use only. Avoid contact with the eyes. In case of contact, wash eyes liberally with water.
2. This medication should not be used for any disorder other than that for which it was prescribed.
3. Patients should promptly report to their physician any worsening of their skin condition.
4. Parents of pediatric patients should be advised not to use Derma-Smoothe/FS® in the treatment of diaper dermatitis. Derma-Smoothe/FS® should not be applied to the diaper area as diapers or plastic pants may constitute occlusive dressing.
5. This medication should not be used on the face, underarm, or groin unless directed by the physician.
6. As with other corticosteroids, therapy should be discontinued when control is achieved. If no improvement is seen within 2 weeks, contact the physician.

Laboratory Tests

The following tests may be helpful in evaluating patients for HPA axis suppression:

ACTH stimulation test
A.M. plasma cortisol test
Urinary free cortisol test

Carcinogenesis, mutagenesis, and impairment of fertility

Long-term animal studies have not been performed to evaluate the carcinogenic potential or the effect on fertility of Derma-Smoothe/FS®. Studies have not been performed to evaluate the mutagenic potential of fluocinolone acetonide, the active ingredient in Derma-Smoothe/FS®. Some corticosteroids have been found to be genotoxic in various genotoxicity tests (i.e. the in vitro human peripheral blood lymphocyte chromosome aberration assay with metabolic activation, the in vivo mouse bone marrow micronucleus assay, the Chinese hamster micronucleus test and the in vitro mouse lymphoma gene mutation assay).

Pregnancy

Teratogenic effects

Pregnancy category C

Corticosteroids have been shown to be teratogenic in laboratory animals when administered systemically at relatively low dosage levels. Some corticosteroids have been shown to be teratogenic after dermal application in laboratory animals.

There are no adequate and well-controlled studies in pregnant women on teratogenic effects from Derma-Smoothe/FS®. Therefore, Derma-Smoothe/FS® should be used during pregnancy only if the potential benefit justifies the potential risk to the fetus.

Nursing Mothers

Systemically administered corticosteroids appear in human milk and could suppress growth, interfere with endogenous corticosteroid production, or cause other untoward effects. It is not known whether topical administration of corticosteroids could result in sufficient systemic absorption to produce detectable quantities in human milk. Because many drugs are excreted in human milk, caution should be exercised when Derma-Smoothe/FS® is administered to a nursing woman.

Pediatric Use

Derma-Smoothe/FS® may be used twice daily for up to 4 weeks in pediatric patients 2 years and older with moderate to severe atopic dermatitis. Derma-Smoothe/FS® should not be applied to the diaper area.

Application to intertriginous areas should be avoided due to the increased possibility of local adverse events such as striae, atrophy, and telangiectasia, which may be irreversible. The smallest amount of drug needed to cover the affected areas should be applied. Long term safety in the pediatric population has not been established.

Derma-Smoothe/FS® is not recommended for use on the face (see ADVERSE REACTIONS section).

Because of a higher ratio of skin surface area to body mass, children are at a greater risk than adults of HPA-axis-suppression when they are treated with topical corticosteroids. They are therefore also at greater risk of glucocorticosteroid insufficiency after withdrawal of treatment and of Cushing's syndrome while on treatment. Adverse effects including striae have been reported with inappropriate use of topical corticosteroids in infants and children. (SEE PRECAUTIONS).

HPA axis suppression, Cushing's syndrome, and intracranial hypertension have been reported in children receiving topical corticosteroids. Children may be more susceptible to systemic toxicity from equivalent doses due to their larger skin surface to body mass ratios. Manifestations of adrenal suppression in children include linear growth retardation, delayed weight gain, low plasma cortisol levels, and absence of response to ACTH stimulation. Manifestations of intracranial hypertension include bulging fontanelles, headaches, and bilateral papilledema.

Derma-Smoothe/FS® is formulated with 48% refined peanut oil NF. Peanut oil used in this product is routinely tested for peanut proteins through amino acid analysis; the quantity of amino acids is below 0.5 parts per million (ppm).

Physicians should use caution in prescribing Derma-Smoothe/FS® for peanut sensitive individuals.

ADVERSE REACTIONS

The following local adverse reactions have been reported infrequently with topical corticosteroids. They may occur more frequently with the use of occlusive dressings, especially with higher potency corticosteroids. These reactions are listed in an approximate decreasing order of occurrence: burning, itching, irritation, dryness, folliculitis, acneiform eruptions, hypopigmentation, perioral dermatitis, allergic contact dermatitis, secondary infection, skin atrophy, striae, and miliaria. One peanut sensitive child experienced a flare of his atopic dermatitis after 5 days of twice daily treatment with Derma-Smoothe/FS®.

A post marketing (open-label) safety study was conducted in 58 children to evaluate the local safety of Derma-Smoothe/FS® when applied twice daily for 4 weeks to the face in children (2 to 12 years) with moderate to severe atopic dermatitis (see Table of Incidence of Adverse Events).

Incidence of Adverse Events (%) N=58
Adverse Event (AE) [The number of individual adverse events reported does not necessarily reflect the number of individual subjects, since one subject could have multiple reporting of an adverse event.] | # of patients (%) | Day 14 | Day 28 [End of Treatment] | Day 56 [Four Weeks Post Treatment]
Any AE | 15 (25.9) | 6 (10.3) | 7 (12.1) | 7 (12.1)
Telangiectasia | 5 (8.6) | 3 (5.2) | 4 (6.9) | 2 (3.5)
Erythema | 3 (5.2) |  |  | 3 (5.2)
Itching | 3 (5.2) |  |  | 3 (5.2)
Irritation | 3 (5.2) |  |  | 3 (5.2)
Burning | 3 (5.2) |  |  | 3 (5.2)
Hypopigmentation | 2 (3.5) | 2 (3.5)
Shiny Skin | 1 (1.7) |  | 1 (1.7)
Secondary atopic dermatitis | 1 (1.7) |  |  | 1 (1.7)
Papules and pustules | 1 (1.7) |  |  | 1 (1.7)
Keratosis pilaris | 1 (1.7) |  |  | 1 (1.7)
Folliculitis | 1 (1.7) |  | 1 (1.7)
Facial herpes simplex | 1 (1.7) | 1 (1.7)
Acneiform eruption | 1 (1.7) |  | 1 (1.7)
Ear infection | 1 (1.7) |  | 1 (1.7)

OVERDOSAGE

Topically applied Derma-Smoothe/FS® can be absorbed in sufficient amounts to produce systemic effects (see PRECAUTIONS).

DOSAGE AND ADMINISTRATION

Derma-Smoothe/FS® for scalp psoriasis in adults (Scalp Oil):

For the treatment of scalp psoriasis, wet or dampen hair and scalp thoroughly. Apply a thin film of Derma-Smoothe/FS® on the scalp, massage well and cover scalp with the supplied shower cap. Leave on overnight or for a minimum of 4 hours before washing off. Wash hair with regular shampoo and rinse thoroughly.

HOW SUPPLIED

Derma-Smoothe/FS® is supplied in bottles containing 4 fluid ounces. It is labeled as Scalp Oil (NDC # 54868-5351-0).

Scalp Oil is supplied with 2 shower caps.

STORAGE AND HANDLING

Keep tightly closed. Store at 25°C (68° to 77°F); excursions permitted to 15°–30°C (59°–86° F) [see USP Controlled Room Temperature].

CAUTION: Rx only

MANUFACTURED and DISTRIBUTED BY:
Hill Dermaceuticals, Inc.
Sanford, Florida 32773

Rev. CODE 171A177
Date: 6/07

Additional barcode labeling by:
Physicians Total Care, Inc.
Tulsa, Oklahoma 74146

PRINCIPAL DISPLAY PANEL - 118.28 mL Label

NDC 54868-5351-0

Rx only

Derma-Smoothe/FS®

Fluocinolone Acetonide
0.01% Topical Oil

(SCALP OIL)

FOR TOPICAL USE ONLY

NOT FOR ORAL, OPHTHALMIC
OR INTRAVAGINAL USE

SHAKE WELL BEFORE USE

Net Contents 118.28 mL
(4 Fl. oz.)